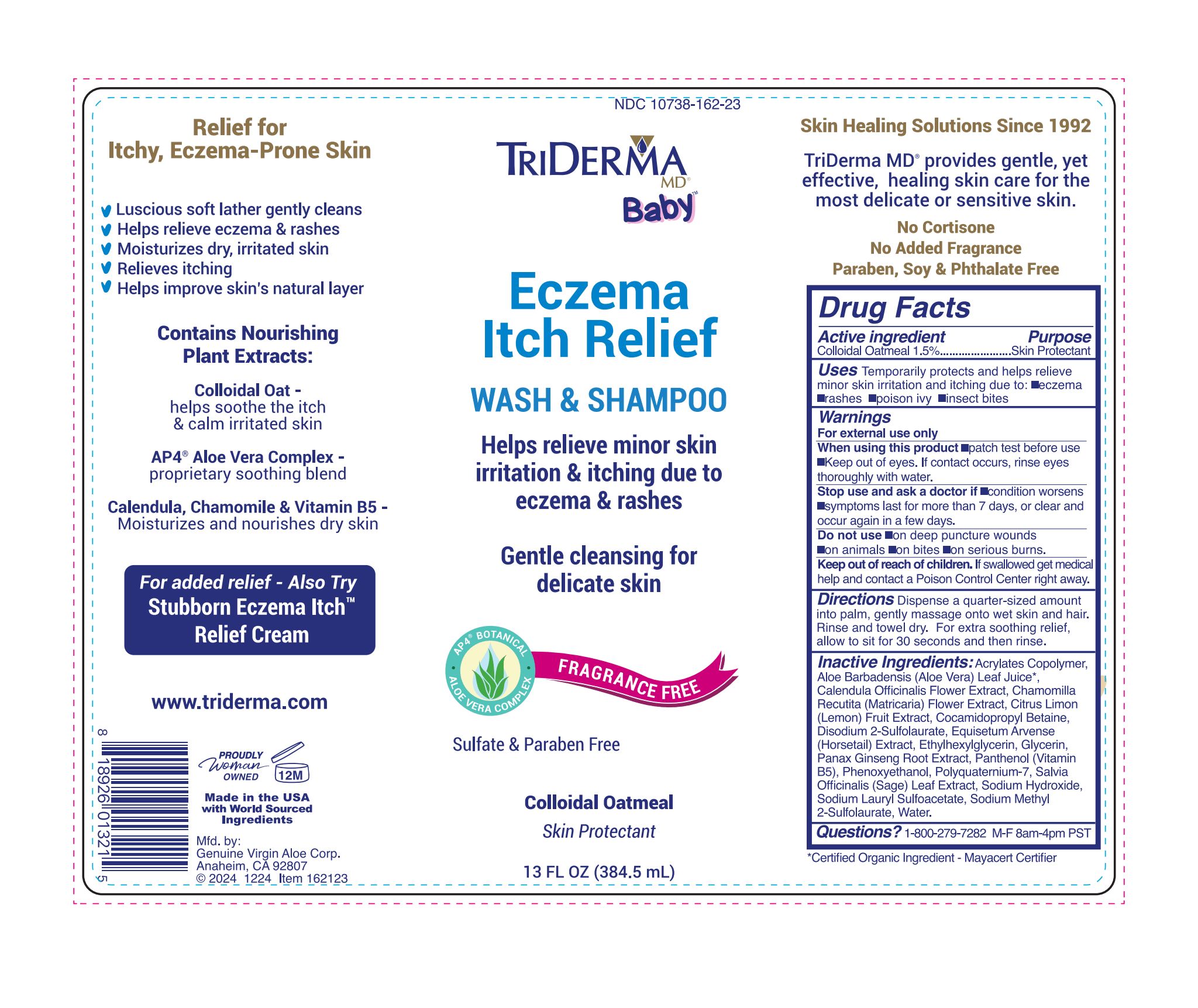 DRUG LABEL: Eczema Itch Relief Wash and Shampo
NDC: 10738-162 | Form: SHAMPOO
Manufacturer: Genuine Virgin Aloe Corporation
Category: otc | Type: HUMAN OTC DRUG LABEL
Date: 20260124

ACTIVE INGREDIENTS: OATMEAL 15 mg/1 mL
INACTIVE INGREDIENTS: SODIUM LAURYL SULFOACETATE; PANAX GINSENG ROOT; ALOE VERA LEAF; GLYCERIN; SODIUM HYDROXIDE; COCAMIDOPROPYL BETAINE; POLYQUATERNIUM-7 (70/30 ACRYLAMIDE/DADMAC; 1600 KD); PHENOXYETHANOL; ETHYLHEXYLGLYCERIN; EQUISETUM ARVENSE BRANCH; SODIUM METHYL 2-SULFOLAURATE; DISODIUM 2-SULFOLAURATE; PANTHENOL; CHAMOMILE; LEMON PEEL; WATER; SAGE; CALENDULA OFFICINALIS FLOWER

TriDerma Eczema Itch Relief Wash and Shampo

Active Ingredient

Colloidal Oatmeal 1.5%

Purpose

Skin Protectant

Uses

Temporarily protects and helps relieve minor skin irritation and itching due to: •eczema •rashes •poison ivy •insect bites

Warnings

For external use only

When using this product • patch test before use • Keep out of eyes. If contact occurs, rinse eyes thoroughly with water.

Stop use and ask a doctor if • condition worsens • symptoms last for more than 7 days, or clear and occur again in a few days

Do not use • on deep puncture wounds • on animals • on bites • on serious burns

Keep out of reach of children. If swallowed get medical help and contact a Poison Control Center right away.

Directions

Dispense a dime to quarter-sized amount into palm, gently massage onto wet skin and hair. Rinse and towel dry. For extra cleansing, allow to sit for 30 seconds and then rinse.

Ingredients

Acrylates Copolymer, Aloe Barbadensis (Aloe Vera) Leaf Juice*, Calendula Officinalis Flower Extract, Chamomilla Recutita (Matricaria) Flower Extract, Citrus Limon (Lemon) Fruit Extract, Cocamidopropyl Betaine, Disodium 2-Sulfolaurate, Equisetum Arvense (Horsetail) Extract, Ethylhexylglycerin, Glycerin, Panax Ginseng Root Extract, Panthenol (Vitamin B5), Phenoxyethanol, Polyquaternium-7, Salvia Officinalis (Sage) Leaf Extract, Sodium Hydroxide, Sodium Lauryl Sulfoacetate, Sodium Methyl 2-Sulfolaurate, Water.

*Certified Organic Ingredient - Mayacert Certifier

Questions?

1-800-279-7282 M-F 8am-4pm PST